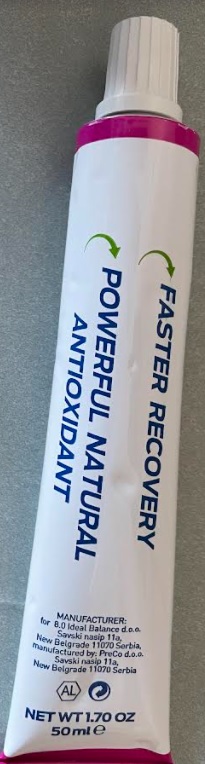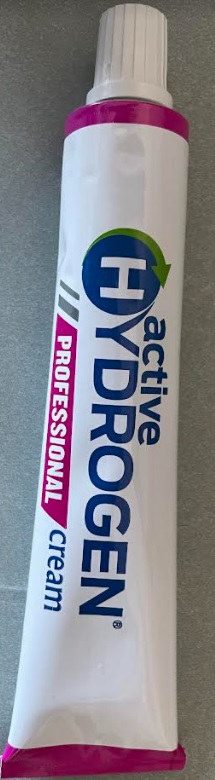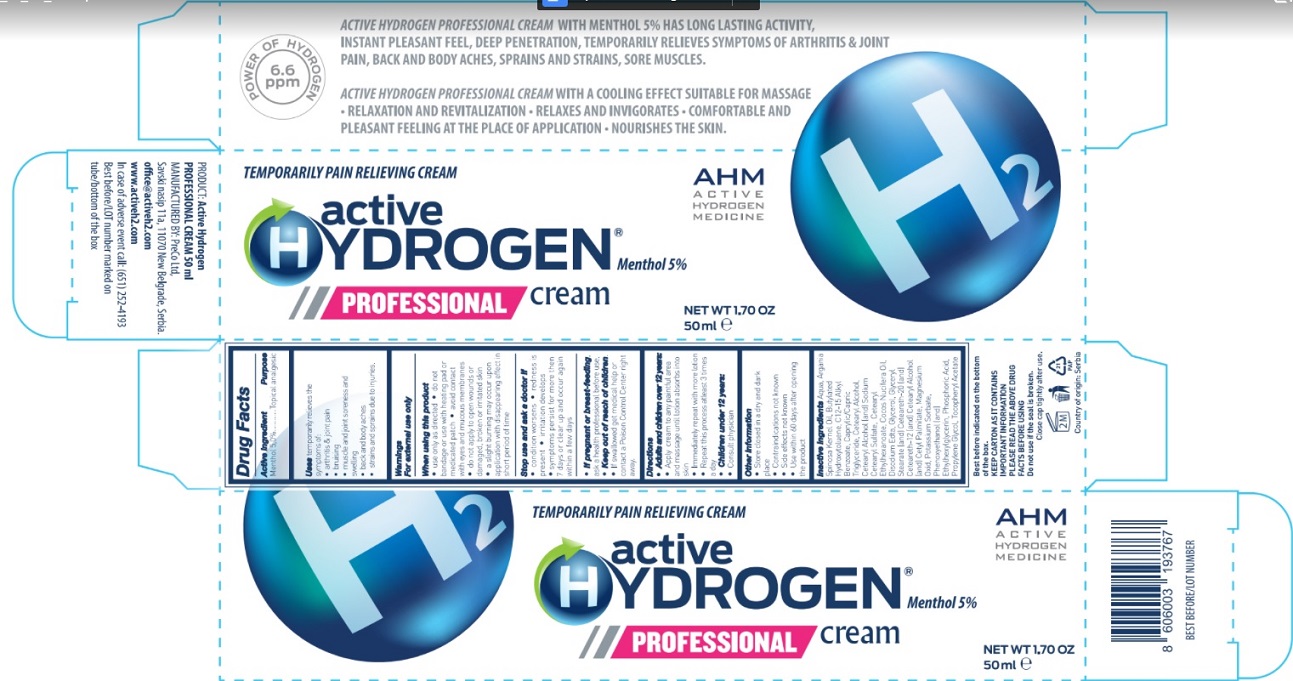 DRUG LABEL: Active HYDROGEN PROFESSIONAL cream
NDC: 72901-002 | Form: CREAM
Manufacturer: 8.0 IDEAL BALANCE D.O.O. BEOGRAD
Category: otc | Type: HUMAN OTC DRUG LABEL
Date: 20220224

ACTIVE INGREDIENTS: MENTHOL 70 mg/1 mL
INACTIVE INGREDIENTS: WATER; GLYCERYL MONOSTEARATE; POLYOXYL 20 CETOSTEARYL ETHER; CETEARETH-12; CETOSTEARYL ALCOHOL; CETYL PALMITATE; GLYCERIN; PROPYLENE GLYCOL; MINERAL OIL; CETEARYL ETHYLHEXANOATE; MEDIUM-CHAIN TRIGLYCERIDES; ALKYL (C12-15) BENZOATE; EDETATE DISODIUM ANHYDROUS; BORIC ACID; PHENOXYETHANOL; ETHYLHEXYLGLYCERIN; ASCORBIC ACID; MAGNESIUM OXIDE; BUTYLATED HYDROXYTOLUENE; ALPHA-TOCOPHEROL ACETATE

Active HYDROGEN PROFESSIONAL cream

Warnings

- For external use only
- When using this product

• use only as directed

• do not bandage or use with heating pad or medicated patch

• avoid contact with eyes and mucous membranes

• do not apply to open wounds or damaged, broken or irritated skin

• a slight burning may occur upon application with disappearing effect in short period of time

Purpose

Topical analgesic

Uses

Reduces and stops the inflammatory process, eliminates pain, reduces swelling, speeds up
recovery process after injuries, neutralizes excretion of lactic acid in the muscles

Directions

adults and children over 12 years:
• apply a thin layer to the target - the sore spot
• massage into painful area until thoroughly absorbed into skin

• repeat the process one again.

• repeat the process minimum 3 times per day

Children 12 years or younger: ask a doctor

KEEP OUT OF REACH OF CHILDREN

If preganant or breast-feeding, ask a health professional before use.

Keep out of reach of children

If swallowed get medical help or contact a Poison Control Center right away

Use within 90 days after opening the product.

Stop use and ask doctor if

• condition worsens

• redness is present

• irritation develops
• symptoms persist for more then 7 days or clear up and occur again within a few days

Inactive Ingredients

Ascorbic Acid, Aqua, Boric Acid, Butylated Hydroxytoluene, C12-15 Alkyl Benzoate, Caprylic/Capric Triglyceride, Cetearyl Alcohol, Cetearyl Ethylhexanoate, Disodium Edta, Glycerol, Glyceryl Stearate (and) Ceteareth-20 (and) Ceteareth-12 (and) Cetearyl Alcohol (and) Cetyl Palmitate, Magnesium Oxide, Paraffinum Liquidum, Perfume, Phenoxyethanol (and) Ethylhexylglycerin, Propylene Glycol, Tocopheryl Acetate.